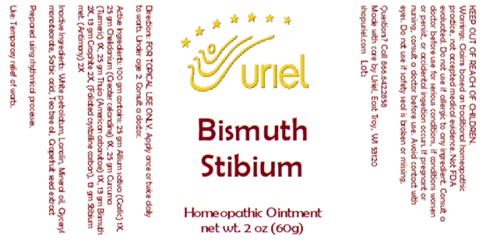 DRUG LABEL: Bismuth Stibium
NDC: 48951-2160 | Form: OINTMENT
Manufacturer: Uriel Pharmacy Inc.
Category: homeopathic | Type: HUMAN OTC DRUG LABEL
Date: 20250430

ACTIVE INGREDIENTS: GARLIC 1 [hp_X]/1 g; CHELIDONIUM MAJUS 1 [hp_X]/1 g; TURMERIC 1 [hp_X]/1 g; THUJA OCCIDENTALIS WHOLE 1 [hp_X]/1 g; BISMUTH 2 [hp_X]/1 g; ANTIMONY 2 [hp_X]/1 g; GRAPHITE 2 [hp_X]/1 g
INACTIVE INGREDIENTS: PETROLATUM; LANOLIN; MINERAL OIL; GLYCERYL MONOSTEARATE; SORBIC ACID; CITRUS PARADISI SEED; TEA TREE OIL

Bismuth Stibium

INDICATIONS AND USAGE

Directions: FOR TOPICAL USE ONLY.

DOSAGE AND ADMINISTRATION

Apply once or twice daily to warts. Under age 2: Consult a doctor

ACTIVE INGREDIENT

Active Ingredients: 100 gm contains: 25 gm Allium sativa (Garlic) 1X, 25 gm Chelidonium (Greater celandine) 1X, 25 gm Curcuma (Turmeric) 1X, 25 gm Thuja (American arborvitae) 1X, 20 gm Bismuth 2X, 20 gm Stibium met. (Antimony) 2X

INACTIVE INGREDIENT

Inactive Ingredients: White petrolatum, Lanolin, Mineral oil, Glyceryl monostearate, Sorbic acid, Tea tree oil, Grapefruit seed extract

Prepared using rhythmical processes.

PURPOSE

Use: Temporary relief of warts.

KEEP OUT OF REACH OF CHILDREN.

WARNINGS

Warnings: Claims based on traditional homeopathic practice, not accepted medical evidence. Not FDA evaluated. Do not use if allergic to any ingredient. Consult a doctor before use for serious conditions, if conditions worsen or persist, or accidental ingestion occurs. If pregnant or nursing, consult a doctor before use. Avoid contact with eyes. Do not use if safety seal is broken or missing.

Questions? Call 866.642.2858
Made with care by Uriel, East Troy, WI 53120
shopuriel.com Lot: